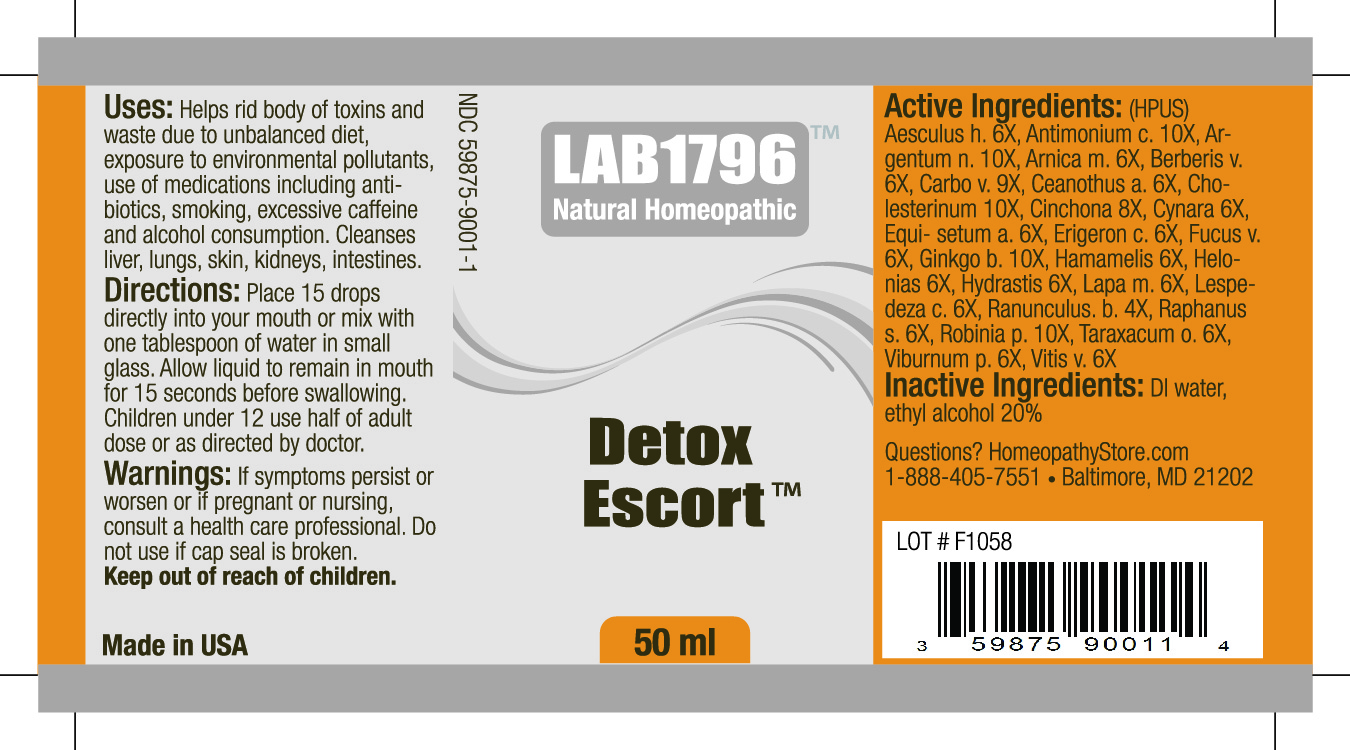 DRUG LABEL: Lab1796 Detox Escort
NDC: 59875-9001 | Form: SOLUTION/ DROPS
Manufacturer: HomeopathyStore.com
Category: homeopathic | Type: HUMAN OTC DRUG LABEL
Date: 20101230

ACTIVE INGREDIENTS: HORSE CHESTNUT 6 [hp_X]/50 mL; ANTIMONY TRISULFIDE 6 [hp_X]/50 mL; SILVER NITRATE 10 [hp_X]/50 mL; ARNICA MONTANA 6 [hp_X]/50 mL; BERBERIS VULGARIS ROOT BARK 6 [hp_X]/50 mL; ACTIVATED CHARCOAL 9 [hp_X]/50 mL; CEANOTHUS AMERICANUS LEAF 6 [hp_X]/50 mL; CHOLESTEROL 10 [hp_X]/50 mL; CINCHONA OFFICINALIS BARK 8 [hp_X]/50 mL; ARTICHOKE 6 [hp_X]/50 mL; EQUISETUM ARVENSE TOP 6 [hp_X]/50 mL; CONYZA CANADENSIS 6 [hp_X]/50 mL; FUCUS VESICULOSUS 6 [hp_X]/50 mL; GINKGO 10 [hp_X]/50 mL; HAMAMELIS VIRGINIANA ROOT BARK/STEM BARK 6 [hp_X]/50 mL; CHAMAELIRIUM LUTEUM ROOT 6 [hp_X]/50 mL; GOLDENSEAL 6 [hp_X]/50 mL; ARCTIUM LAPPA ROOT 6 [hp_X]/50 mL; LESPEDEZA CAPITATA FLOWERING TOP 6 [hp_X]/50 mL; RANUNCULUS BULBOSUS 4 [hp_X]/50 mL; DAIKON 6 [hp_X]/50 mL; ROBINIA PSEUDOACACIA BARK 10 [hp_X]/50 mL; TARAXACUM OFFICINALE 6 [hp_X]/50 mL; VIBURNUM PRUNIFOLIUM BARK 6 [hp_X]/50 mL; WINE GRAPE 6 [hp_X]/50 mL
INACTIVE INGREDIENTS: WATER; ALCOHOL

Detox Escort

Uses:

Helps rid body of toxins and waste due to unbalanced diet, exposure to environmental pollutants, use of medications including antibiotics, smoking, excessive caffeine and alcohol consumption. Cleanses liver, lungs, skin, kidneys, intestines.

Directions:

DOSAGE AND ADMINISTRATION

Place 15 drops directly into your mouth or mix with one tablespoon of water in small glass. Allow liquid to remain in mouth for 15 seconds before swallowing. Children under 12 use half of adult dose or as directed by doctor.

Warnings:

If symptoms persist or worsen or if pregnant or nursing, consult a health care professional. Do not use if cap seal is broken.

Keep out of reach of children.

Active Ingredients:

(HPUS) Aesculus h. 6X, Antimonium c. 10X, Argentum n. 10X, Arnica m. 6X, Berberis v. 6X, Carbo v. 9X, Ceanothus a. 6X, Cholesternium 10X, Cinchona 8X, Cynara 6X, Equisetum a. 6X, Erigeron c. 6X, Fucus v. 6X, Ginkgo b. 10X, Hamamelis 6X, Helonias 6X, Hydrastis 6X, Lappa m. 6X, Lespedeza c. 6X, Ranunculus b. 4X, Raphanus s. 6X, Robinia p. 10X, Taraxacum o. 6X, Viburnum p. 6X, Vitis v. 6X

Inactive Ingredients:

DI water, ethyl alcohol 20%